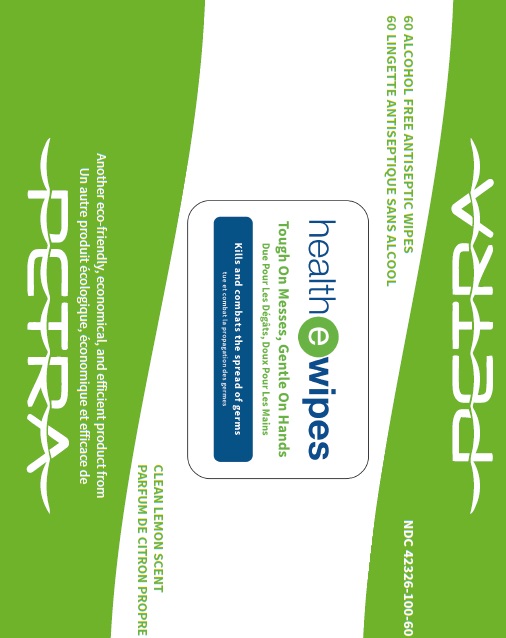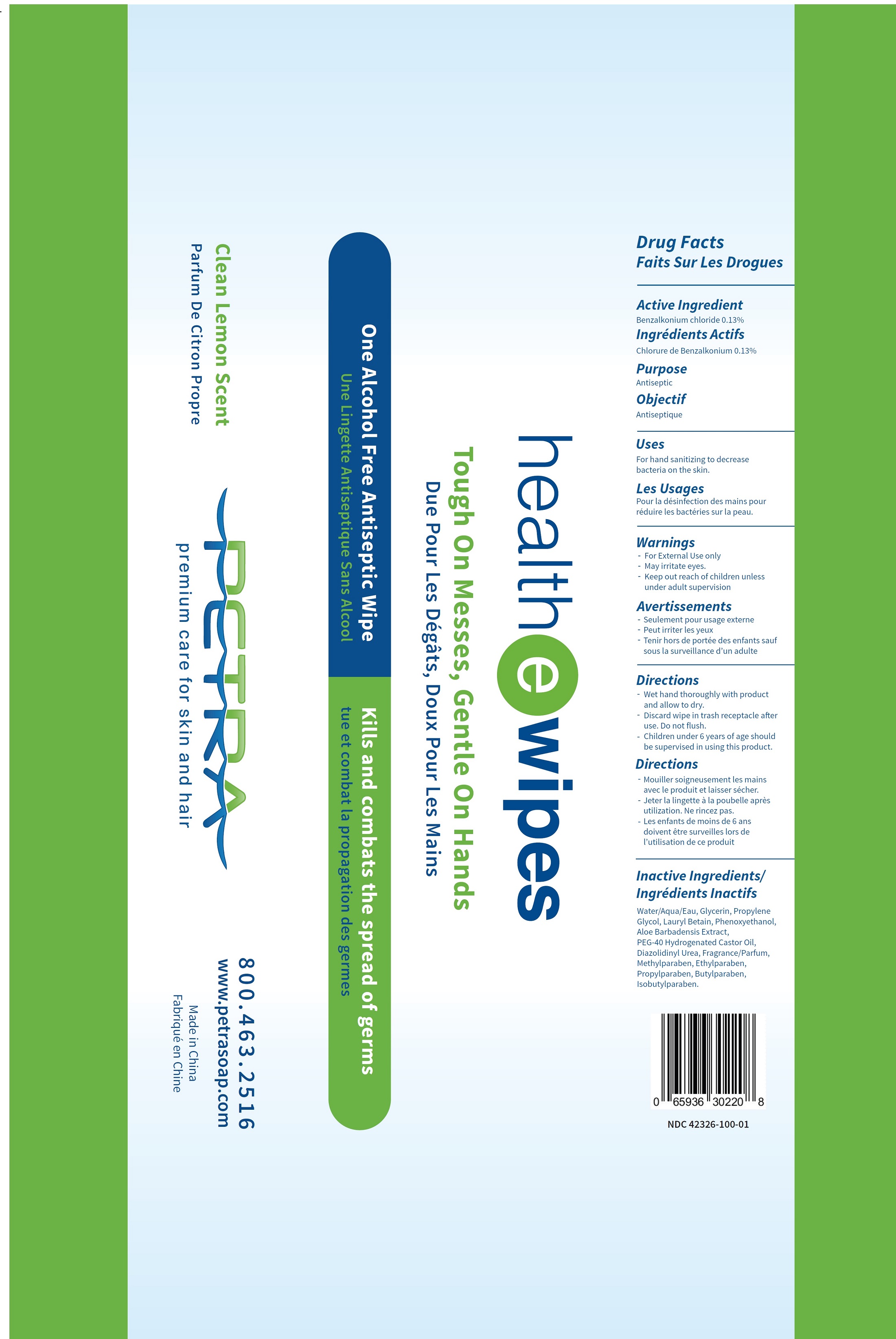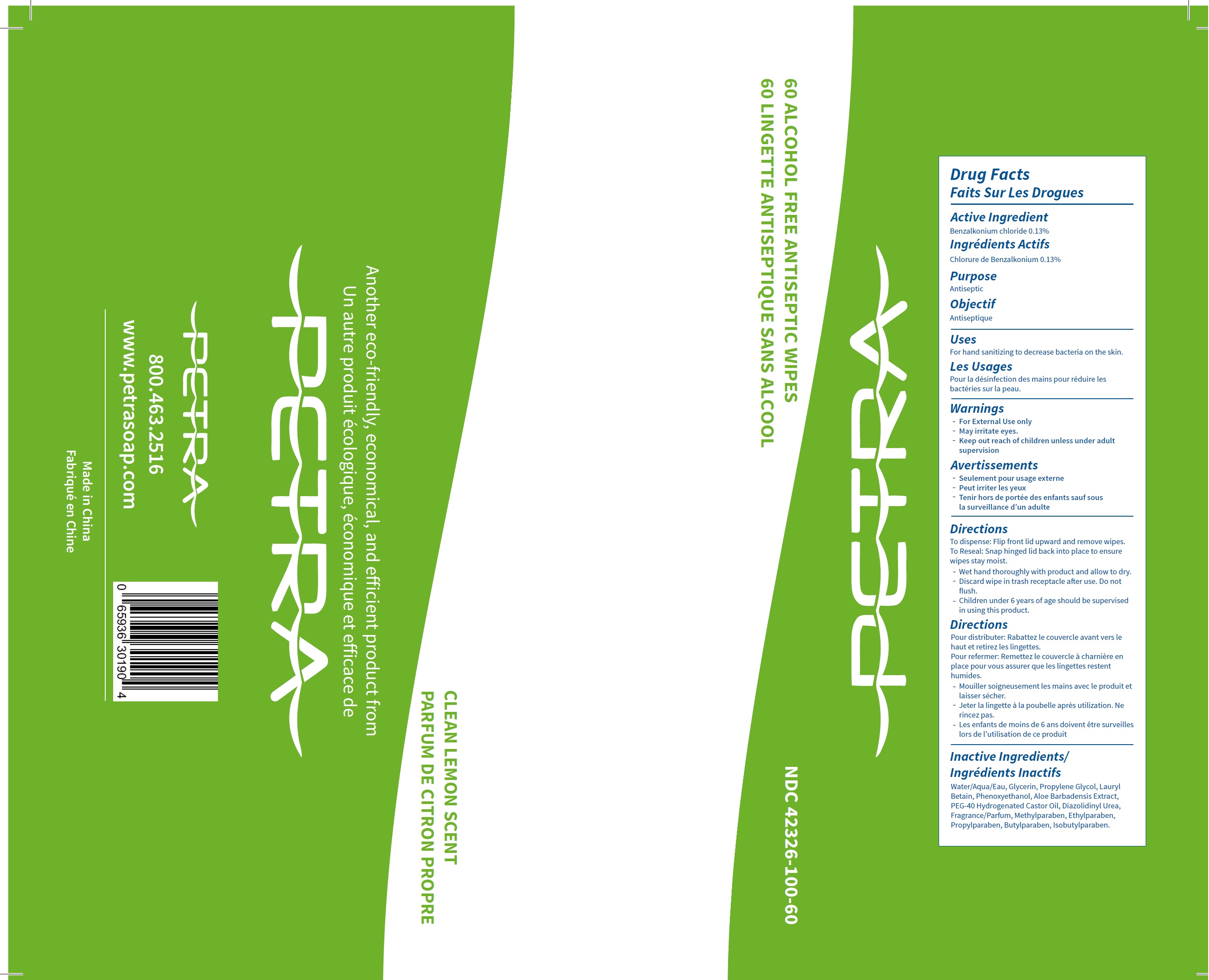 DRUG LABEL: Petra Health E Wipes Alcohol Free Antiseptic
NDC: 42326-100 | Form: CLOTH
Manufacturer: Petra Hygienic Systems Int Ltd
Category: otc | Type: HUMAN OTC DRUG LABEL
Date: 20250717

ACTIVE INGREDIENTS: BENZALKONIUM CHLORIDE 1.3 mg/1 mL
INACTIVE INGREDIENTS: WATER; GLYCERIN; PROPYLENE GLYCOL; LAURYL BETAINE; PHENOXYETHANOL; ALOE VERA LEAF; POLYOXYL 40 HYDROGENATED CASTOR OIL; DIAZOLIDINYL UREA; METHYLPARABEN; ETHYLPARABEN; PROPYLPARABEN; BUTYLPARABEN; ISOBUTYLPARABEN

Petra Health-E-Wipes Alcohol Free Antiseptic Wipes

Active Ingredient

Benzalkonium chloride 0.13%

Purpose

Antiseptic

Uses

For hand sanitizing to decrease bacteria on the skin.

Warnings

- For external use only
- May irritate eyes

Keep out reach of children

unless under adult supervision

Directions

To dispense: Flip front lid unward and remove wipes. To Reseal: Snap hinged lid back into place to ensure wipes stay moist.

Wet hand thoroughly with product and allow to dry.

Discard wipe in trash receptacle after use. Do not flush.

Children under 6 years of age should be supervised in using this product.

Inactive Ingredients

Water/Aqua/Eau, Glycerin, Propylene Glycol, Lauryl Betain, Phenoxyethanol, Aloe Barbadensis Extract, PEG-40 Hydrogenated Castor Oil, Diazolidinyl Urea, Fragrance/Parfum, Methylparaben, Ethylparaben, Propylparaben, Butylparaben, Isobutylparaben.